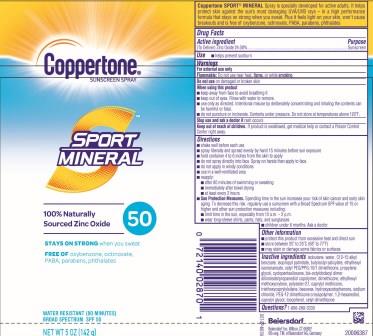 DRUG LABEL: Coppertone Sport Mineral Sunscreen SPF 50
NDC: 66800-4724 | Form: AEROSOL, SPRAY
Manufacturer: Beiersdorf Inc
Category: otc | Type: HUMAN OTC DRUG LABEL
Date: 20251231

ACTIVE INGREDIENTS: ZINC OXIDE 240.8 mg/1 g
INACTIVE INGREDIENTS: ISOBUTANE; ETHYLHEXYL ISONONANOATE; TRIETHOXYCAPRYLYLSILANE; ALKYL (C12-15) BENZOATE; BIS-OCTYLDODECYL DIMER DILINOLEATE/PROPANEDIOL COPOLYMER; CAPRYLYL TRISILOXANE; 1,2-HEXANEDIOL; ISOPROPYL PALMITATE; BUTYLOCTYL SALICYLATE; HYDROXYACETOPHENONE; POLYESTER-7; PROPYLENE GLYCOL; CYCLOMETHICONE 5; DIMETHICONE 1000; CETYL DIMETHICONE 150; CAPRYLYL GLYCOL; CETYL PEG/PPG-10/1 DIMETHICONE (HLB 2); PEG-12 DIMETHICONE; ETHYLHEXYL METHOXYCRYLENE; SYNTHETIC BEESWAX; SODIUM CHLORIDE

Coppertone Sport Mineral Spray SPF 50

Drug Facts

Active Ingredient

(To Deliver) Zinc Oxide 24.08%

Purpose

Sunscreen

Use

helps prevent sunburn

Warnings

For external use only
Flammable:Do not use near heat, flame, or while smoking

Do not useon damaged or broken skin

WHEN USING

■ keep away from face to avoid breathing it

■ keep out of eyes. Rinse with water to remove.

■ use only as directed. Intentional misuse by deliberately concentrating and inhaling the contents can be harmful or fatal.

■ do not puncture or incinerate. Contents under pressure. Do not store at temperatures above 120˚F.

Keep out of reach of children.If product is swallowed, get medical help or contact a Poison Control Center right away.

Stop use and ask a doctor ifrash occurs

Directions

■ shake well before each use

■ spray liberally and spread evenly by hand 15 minutes before sun exposure

■ hold container 4 to 6 inches from the skin to apply

■ do not spray directly into face. Spray on hands then apply to face.

■ do not apply in windy conditions

■ use in a well-ventilated area

■ reapply:

■ after 80 minutes of swimming or sweating

■ immediately after towel drying

■ at least every 2 hours

■ Sun Protection Measures. Spending time in the sun increases your risk of skin cancer and early skin aging. To decrease this risk, regularly use a sunscreen with a Broad Spectrum SPF value of 15 or higher and other sun protection measures including:

■ limit time in the sun, especially from 10 a.m. – 2 p.m.

■ wear long-sleeve shirts, pants, hats, and sunglasses

■ children under 6 months: Ask a doctor

Other Information

■ protect this product from excessive heat and direct sun

■ store between 20˚ to 25˚C (68˚ to 77˚F)

■ may stain or damage some fabrics or surfaces

Inactive Ingredients

isobutane, water, C12-15 alkyl benzoate, isopropyl palmitate, butyloctyl salicylate, ethylhexyl isononanoate, cetyl PEG/PPG-10/1 dimethicone, propylene glycol, cyclopentasiloxane, bis-octyldodecyl dimer dilinoleate/propanediol copolymer, dimethicone, ethylhexyl methoxycrylene, polyester-27, caprylyl methicone, triethoxycaprylylsilane, beeswax, hydroxyacetophenone, sodium chloride, PEG-12 dimethicone crosspolymer, 1,2-hexanediol, caprylyl glycol, tocopherol, cetyl dimethicone

Questions?

1-866-288-3330

PACKAGE LABEL

Coppertone®Sunscreen Spray

Sport Mineral

1 00% Naturally Sourced Zinc Oxide 50

Stays on Strongwhen you sweat

Free Ofoxybenzone, octinoxate, PABA, parabens, phthalates

Water Resistant(80 minutes)

Broad SpectrumSPF 50

NET WT 5 OZ (142 g)